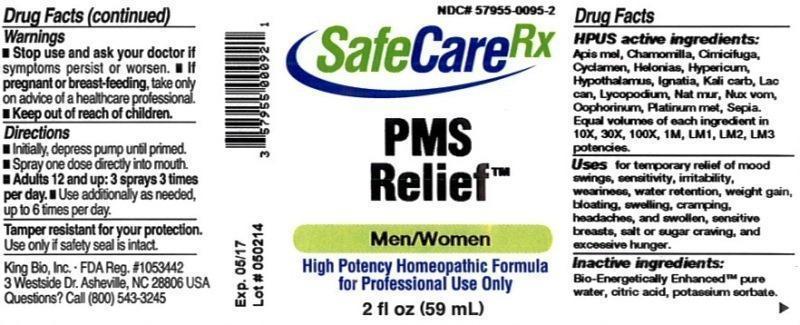 DRUG LABEL: PMS Relief
NDC: 57955-0095 | Form: LIQUID
Manufacturer: King Bio Inc.
Category: homeopathic | Type: HUMAN OTC DRUG LABEL
Date: 20140613

ACTIVE INGREDIENTS: APIS MELLIFERA 10 [hp_X]/59 mL; MATRICARIA RECUTITA 10 [hp_X]/59 mL; BLACK COHOSH 10 [hp_X]/59 mL; CYCLAMEN PURPURASCENS TUBER 10 [hp_X]/59 mL; CHAMAELIRIUM LUTEUM ROOT 10 [hp_X]/59 mL; HYPERICUM PERFORATUM 10 [hp_X]/59 mL; BOS TAURUS HYPOTHALAMUS 10 [hp_X]/59 mL; STRYCHNOS IGNATII SEED 10 [hp_X]/59 mL; POTASSIUM CARBONATE 10 [hp_X]/59 mL; CANIS LUPUS FAMILIARIS MILK 10 [hp_X]/59 mL; LYCOPODIUM CLAVATUM SPORE 10 [hp_X]/59 mL; SODIUM CHLORIDE 10 [hp_X]/59 mL; STRYCHNOS NUX-VOMICA SEED 10 [hp_X]/59 mL; SUS SCROFA OVARY 10 [hp_X]/59 mL; PLATINUM 10 [hp_X]/59 mL; SEPIA OFFICINALIS JUICE 10 [hp_X]/59 mL
INACTIVE INGREDIENTS: WATER; CITRIC ACID MONOHYDRATE; POTASSIUM SORBATE

PMS Relief™

ACTIVE INGREDIENT

Drug Facts__________________________________________________________________________________________________________

HPUS active ingredients: Apis mellifica, Chamomilla, Cimicifuga racemosa, Cyclamen europaeum, Helonias dioica, Hypericum perforatum, Hypothalamus, Ignatia amara, Kali carbonicum, Lac caninum, Lycopodium clavatum, Natrum muriaticum, Nux vomica, Oophorinum, Platinum metallicum, Sepia. Equal volumes of each ingredient in 10X, 30X, 100X, 1M, LM1, LM2, LM3 potencies.

INDICATIONS AND USAGE

Uses for temporary relief of mood swings, sensitivity, irritability, weariness, water retention, weight gain, bloating, swelling, cramping, headaches, and swollen, sensitive breasts, salt or sugar craving, and excessive hunger.

Inactive Ingredients:

Bio-Energetically Enhanced™ pure water, citric acid and potassium sorbate.

Warnings

- Stop use and ask your doctor if symptoms persist or worsen.
- If pregnant or breast-feeding, take only on advice of a healthcare professional.

- Keep out of reach of children.

Directions

- Initially, depress pump until primed.
- Spray one dose directly into mouth.
- Adults 12 and up: 3 sprays 3 times per day.
- Use additionally as needed, up to 6 times per day.

OTHER SAFETY INFORMATION

Tamper resistant for your protection. Use only if safety seal is intact.

PURPOSE

Uses for temporary relief of:

- mood swings
- sensitivity
- irritability
- weariness
- water retention
- weight gain
- bloating
- swelling
- cramping
- headaches
- swollen, sensitive breasts
- salt or sugar craving
- excessive hunger